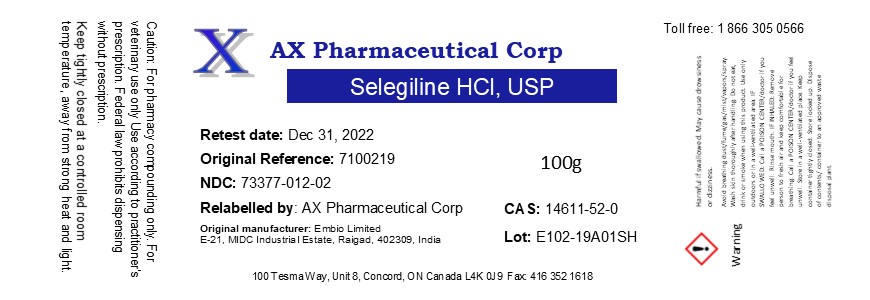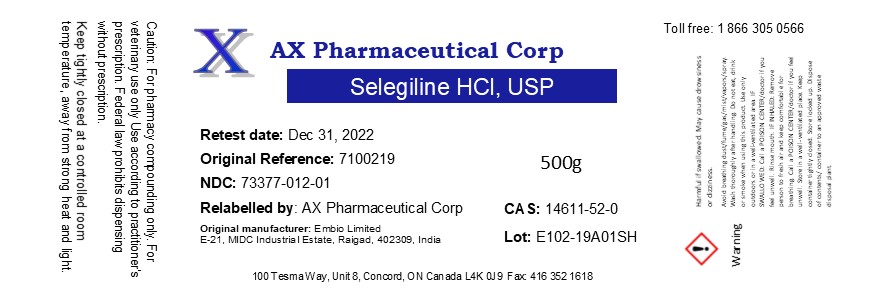 DRUG LABEL: Selegiline Hydrochloride
NDC: 73377-012 | Form: POWDER
Manufacturer: AX Pharmaceutical Corp
Category: other | Type: BULK INGREDIENT
Date: 20200204

ACTIVE INGREDIENTS: SELEGILINE HYDROCHLORIDE 1 g/1 g

Selegiline Hydrochloride